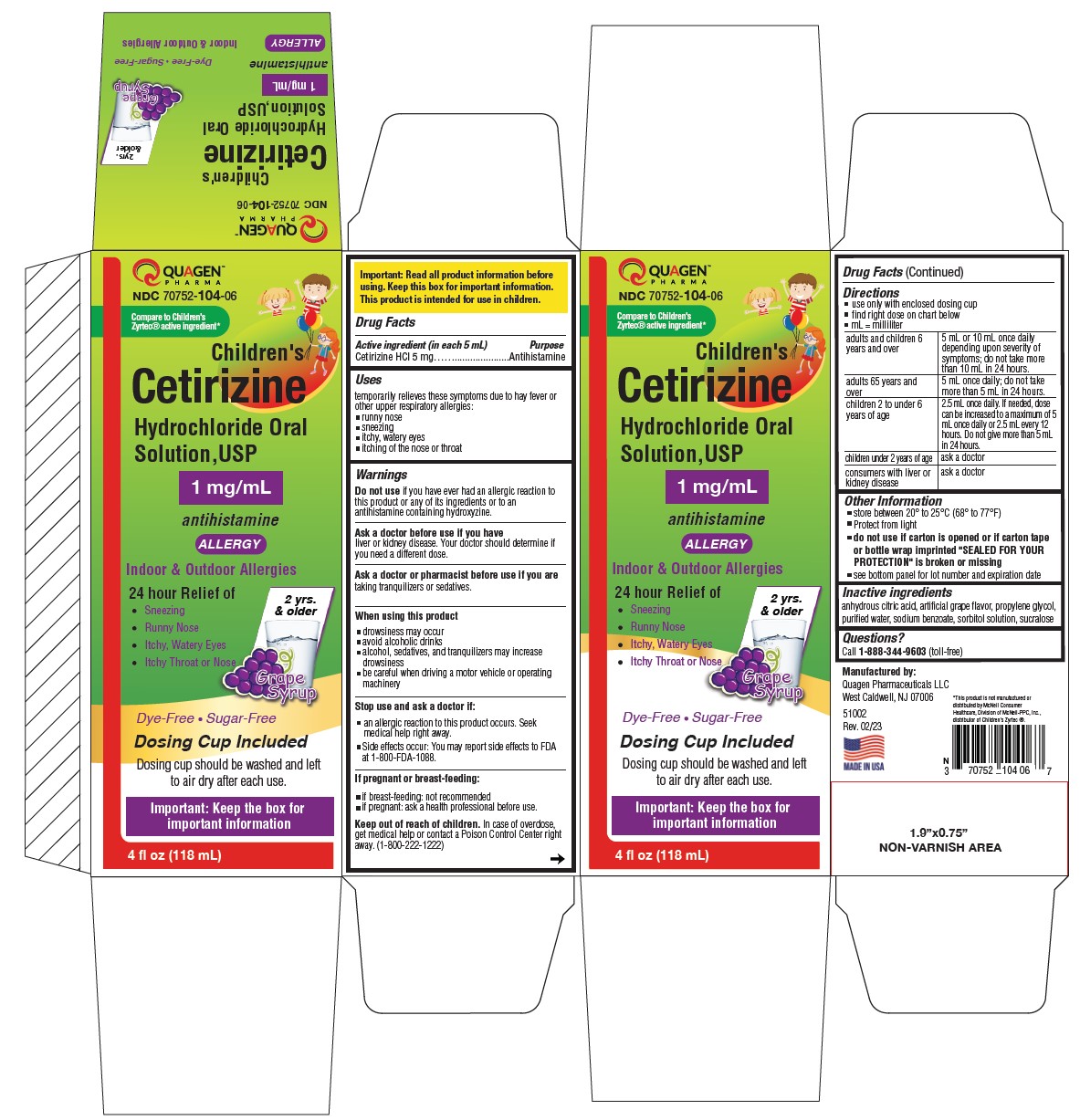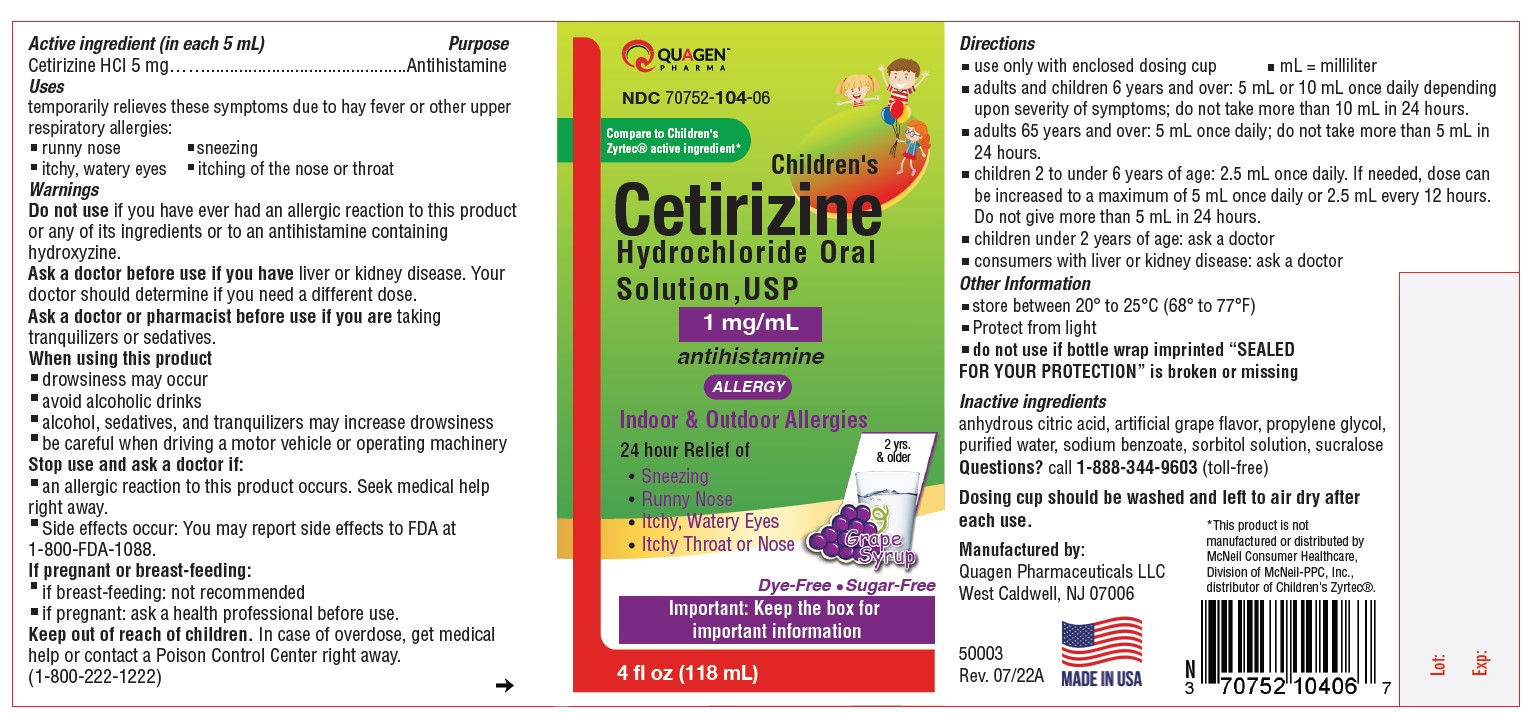 DRUG LABEL: CETIRIZINE HYDROCHLORIDE
NDC: 70752-103 | Form: SOLUTION
Manufacturer: QUAGEN PHARMACEUTICALS LLC
Category: otc | Type: HUMAN OTC DRUG LABEL
Date: 20251226

ACTIVE INGREDIENTS: CETIRIZINE HYDROCHLORIDE 1 mg/1 mL
INACTIVE INGREDIENTS: ANHYDROUS CITRIC ACID; PROPYLENE GLYCOL; WATER; SODIUM BENZOATE; SORBITOL; SUCRALOSE

Children's Cetirizine Hydrochloride Oral Solution, USP 1 mg/mL (Bubble Gum & Grape Flavor)
Important: Read all product information before using. Keep this box for important information. This product is intended for use in children.
DRUG FACTS

Active ingredient (in each 5 mL)

Cetirizine HCl 5 mg

Purpose

Antihistamine

Uses

temporarily relieves these symptoms due to hay fever or other upper respiratory allergies:

- runny nose
- sneezing
- itchy, watery eyes
- itching of the nose or throat

Warnings

Do not use if you have ever had an allergic reaction to this product or any of its ingredients or to an antihistamine containing hydroxyzine.

Ask a doctor before use if you have

liver or kidney disease. Your doctor should determine if you need a different dose.

Ask a doctor or pharmacist before use if you are

taking tranquilizers or sedatives.

When using this product

- drowsiness may occur
- avoid alcoholic drinks
- alcohol, sedatives, and tranquilizers may increase drowsiness
- be careful when driving a motor vehicle or operating machinery

Stop use and ask a doctor if:

- an allergic reaction to this product occurs. Seek medical help right away.
- Side effects occur: You may report side effects to FDA at 1-800-FDA-1088.

If pregnant or breast-feeding:

- if breast-feeding: not recommended
- if pregnant: ask a health professional before use.

Keep out of reach of children. In case of overdose, get medical help or contact a Poison Control Center right away. (1-800-222-1222)

Directions

- use only with enclosed dosing cup
- find right dose on chart below
- mL = milliliter

adults and children 6 years and over | 5 mL or 10 mL once daily depending upon severity of symptoms; do not take more than 10 mL in 24 hours.
adults 65 years and over | 5 mL once daily; do not take more than 5 mL in 24 hours.
children 2 to under 6 years of age | 2.5 mL once daily. If needed, dose can be increased to a maximum of 5 mL once daily or 2.5 mL every 12 hours. Do not give more than 5 mL in 24 hours.
children under 2 years of age | ask a doctor
consumers with liver or kidney disease | ask a doctor

Other Information

- store between 20° to 25°C (68° to 77°F)
- Protect from light
- do not use if carton is opened or if carton tape or bottle wrap imprinted "SEALED FOR YOUR PROTECTION" is broken or missing
- see bottom panel for lot number and expiration date

Inactive ingredients

Bubble Gum Syrup: anhydrous citric acid, artificial bubble gum flavor, propylene glycol, purified water, sodium benzoate, sorbitol solution, sucralose

Grape Syrup: anhydrous citric acid, artificial grape flavor, propylene glycol, purified water, sodium benzoate, sorbitol solution, sucralose

Questions?

Call 1-888-344-9603 (toll-free)

Manufactured by:
Quagen Pharmaceuticals LLC
West Caldwell, NJ 07006
51001 & 51002
Rev. 10/18